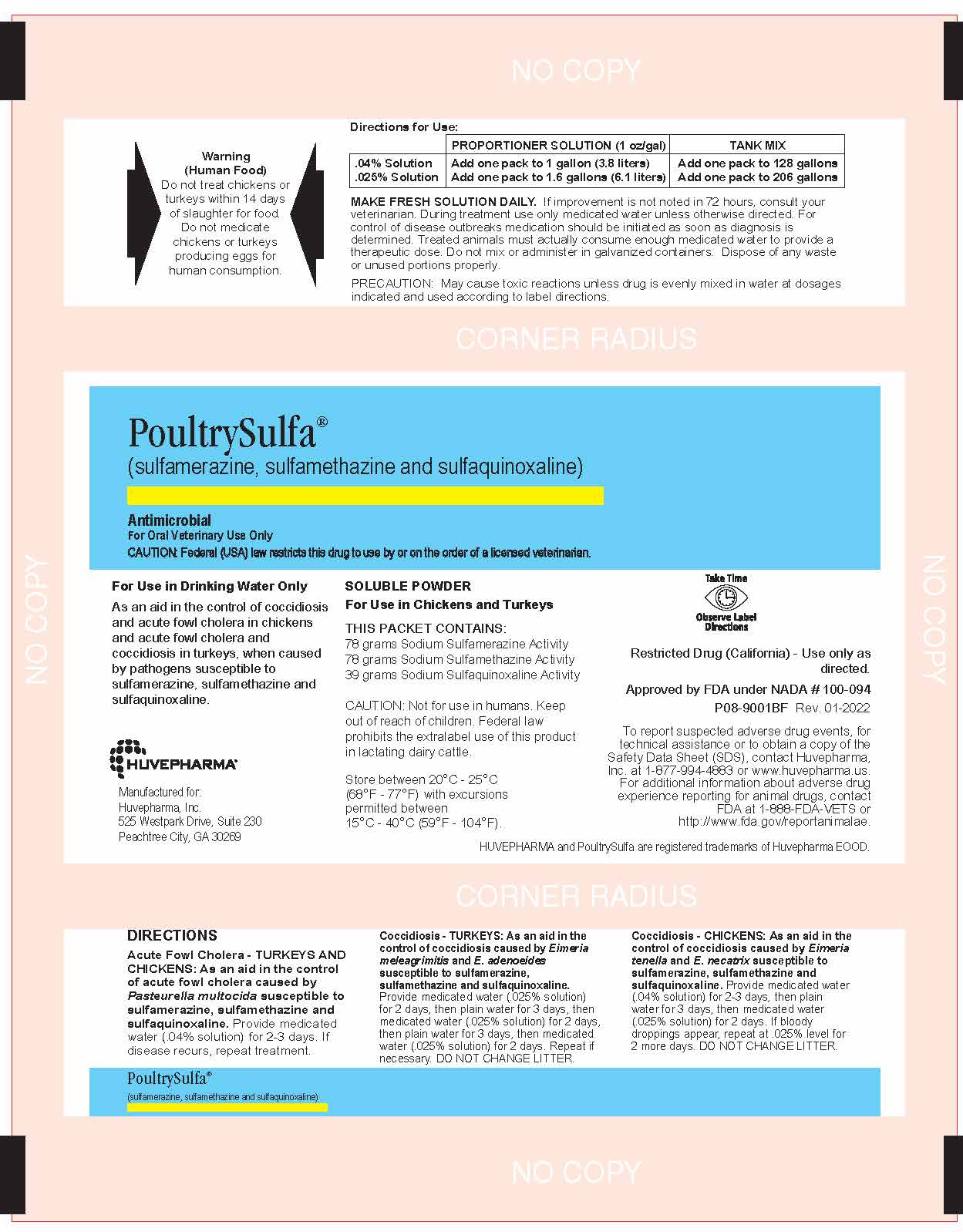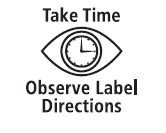 DRUG LABEL: PoultrySulfa
NDC: 23243-6764 | Form: POWDER, FOR SOLUTION
Manufacturer: Huvepharma, Inc
Category: animal | Type: PRESCRIPTION ANIMAL DRUG LABEL
Date: 20230814

ACTIVE INGREDIENTS: SULFAMETHAZINE SODIUM 78 g/195 g; SULFAMERAZINE SODIUM 78 g/195 g; SULFAQUINOXALINE SODIUM 39 g/195 g

PoultrySulfa

PoultrySulfa®

(sulfamerazine, sulfamethazine and sulfaquinoxaline)

Antimicrobial
For Oral Veterinary Use Only

GENERAL PRECAUTIONS

CAUTION: Federal (USA) law restricts this drug to use by or on the order of a licensed veterinarian.

INDICATIONS AND USAGE

For Use in Drinking Water Only

As an aid in the control of coccidiosis and acute fowl cholera in chickens and acute fowl cholera
and coccidiosis in turkeys, when caused by pathogens susceptible to sulfamerazine, sulfamethazine
and sulfaquinoxaline.

SOLUBLE POWDER

For Use in Chickens and Turkeys

THIS PACKET CONTAINS:
78 grams Sodium Sulfamerazine Activity
78 grams Sodium Sulfamethazine Activity
39 grams Sodium Sulfaquinoxaline Activity

GENERAL PRECAUTIONS

CAUTION:

Not for use in humans. Keep out of reach of children. Federal law prohibits the extralabel use of
this product in lactating dairy cattle.

STORAGE AND HANDLING

HUVEPHARMA®

Manufactured for:
Huvepharma, Inc
525 Westpark Drive, Suite 230
Peachtree City, GA 30269

Store between 20°C - 25°C
(68°F- 77°F) with excusions permitted
between 15°C - 40°C (59°F - 104°F).

Restricted Drug (California) - Use only as directed.

Approved by FDA under NADA #100-094

P08-9001BF Rev. 01-2022

ADVERSE REACTIONS

To report suspected adverse drug events, for technical assistance or to obtain a copy of the
Safety Data Sheet (SDS), contact Huvepharma, Inc. at 1-877-994-4883 or www.huvepharma.us.
For additional information about adverse drug experience reporting for animal drugs, contact
FDA at 1-888-FDA-VETS or http://www.fda.gov/reportanimalae.

HUVEPHARMA and PoultrySulfa are registered trademarks of Huvepharma EOOD.

DIRECTIONS

Acute Fowl Cholera - TURKEYS AND CHICKENS: As an aid in the control
of acute fowl cholera caused by Pasteurella multocida susceptible to
sulfamerazine, sulfamethazine and sulfaquinoxaline. Provide medicated
water (.04% solution) for 2-3 days. If disease recurs, repeat treatment.

Coccidiosis - TURKEYS: As an aid in the control of coccidiosis caused by Eimeria
meleagrimitis and E. adenoeides susceptible to sulfamerazine, sulfamethazine
and sulfaquinoxaline. Provide medicated water (.025% solution) for 2 days, then
plain water for 3 days, then medicated water (.025% solution) for 2 days,
then plain water for 3 days, then medicated water (.025% solution) for 2 days.
Repeat if necessary. DO NOT CHANGE LITTER.

Coccidiosis - CHICKENS: As an aid in the control of coccidiosis caused by Eimeria
tenella and E. necatrix susceptible to sulfamerazine, sulfamethazine and
sulfaquinoxaline. Provide medicated water (.04% solution) for 2-3 days, then plain
water for 3 days, then medicated water (.025% solution) for 2 days. If bloody
droppings appear, repeat at .025% level for 2 more days. DO NOT CHANGE LITTER.

PoultrySulfa®
(sulfamerazine, sulfamethazine and sulfaquinoxaline)

WARNINGS

Warning (Human Food)

Do not treat chickens or turkeys within 14 days of slaughter for food.
Do not medicate chickens or turkeys producing eggs for human consumption.

Directions for Use:

 | PROPORTIONER SOLUTION (1 oz/gal) | TANK MIX
.04% Solution.025% Solution | Add one pack to 1 gallon (3.8 liters) Add one pack to 1.6 gallons (6.1 liters) | Add one pack to 128 gallonsAdd one pack to 206 gallons

MAKE FRESH SOLUTION DAILY. If improvement is not noted in 72 hours, consult your veterinarian.
During treatment use only medicated water unless otherwise directed. For control of disease outbreaks
medication should be initiated as soon as diagnosis is determined. Treated animals must actually
consume enough medicated water to provide a therapeutic dose. Do not mix or administer in
galvanized containers. Dispose of any waste or unused portions properly.

PRECAUTIONS

PRECAUTION: May cause toxic reactions unless drug is evenly mixed in water at dosages indicated and used
according to label directions.